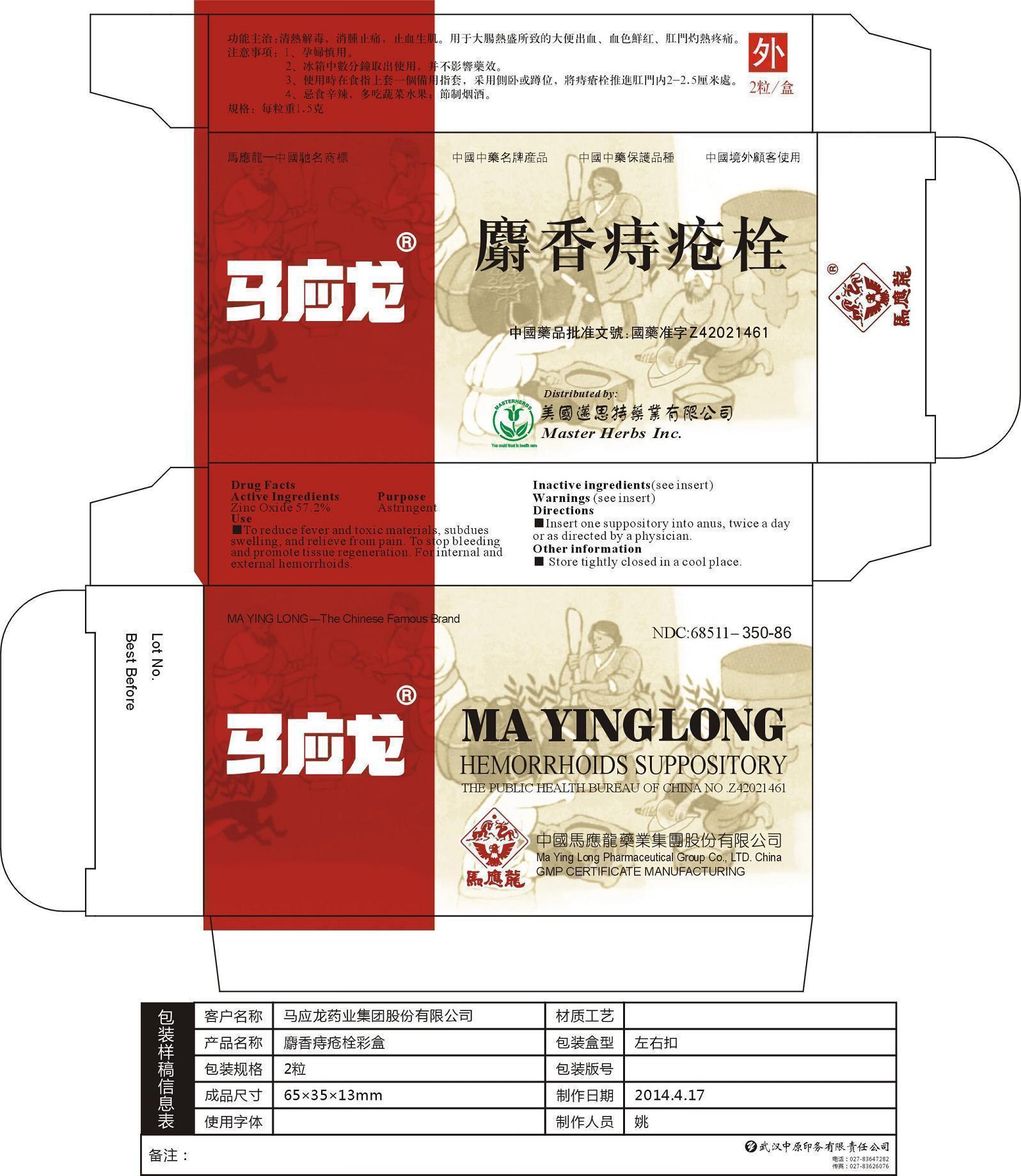 DRUG LABEL: Mayinglong Hemorrhoids
NDC: 68511-350 | Form: SUPPOSITORY
Manufacturer: Mayinglong Pharmaceutical Group Co., Ltd
Category: otc | Type: HUMAN OTC DRUG LABEL
Date: 20140523

ACTIVE INGREDIENTS: ZINC OXIDE 1.7 g/1 1
INACTIVE INGREDIENTS: MUSK KETONE; HYRIOPSIS CUMINGII WHOLE; BORNEOL; PANAX NOTOGINSENG ROOT; BELLADONNA LEAF; RHUS CHINENSIS WHOLE; DIACETYLTARTARIC AND FATTY ACID ESTERS OF GLYCEROL

Mayinglong Hemorrhoids

Active Ingredients

Zinc Oxide 57.2%

Purpose

Zinc Oxide Astrigent

Uses

To reduce fever and toxic materials, subduces swelling, and relieve from pain. To stop bleeding and promote tissue regeneration. For internal and external hemorrhoids.

Warning

Not for oral use.

Immerse it into cool water if it has softened during high temperature.

Eat more vegetables and fruits, avoid constipation, restrict cigarettes, wine and spicy foods.

Warning

Keep out of reach of children.

Warning

Apply it carefully during pregancy or as directed by a physician.

Directions

Insert one suppository into anus, twice a day or as directed by a physician.

Storage

Store tightly closed in a cool place.

Inactive Ingredients

Musk Ketone, Hyriopsis Cumingii Whole, Borneol, Panax Rotoginseng Root, Belladonna Leaf, Rhus Chinensis Whole, Diacetyltartaric and Fatty Acid Esters of Glycerol